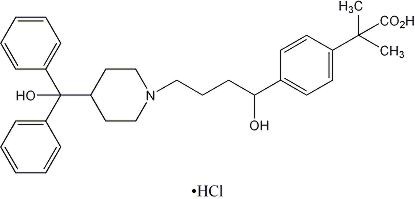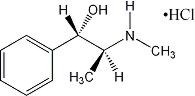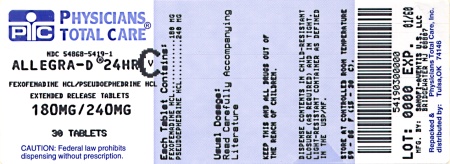 DRUG LABEL: Allegra--D 24 Hour
NDC: 54868-5419 | Form: TABLET, FILM COATED, EXTENDED RELEASE
Manufacturer: Physicians Total Care, Inc.
Category: prescription | Type: HUMAN PRESCRIPTION DRUG LABEL
Date: 20120925
DEA Schedule: CV

ACTIVE INGREDIENTS: FEXOFENADINE HYDROCHLORIDE 180 mg/1 1; PSEUDOEPHEDRINE HYDROCHLORIDE 240 mg/1 1
INACTIVE INGREDIENTS: CELLULOSE, MICROCRYSTALLINE; SODIUM CHLORIDE; CELLULOSE ACETATE; POLYETHYLENE GLYCOLS; POVIDONE; TALC; HYPROMELLOSES; CROSCARMELLOSE SODIUM; COPOVIDONE; TITANIUM DIOXIDE; MAGNESIUM STEARATE; SILICON DIOXIDE; FD&C BLUE NO. 1; ALUMINUM OXIDE; ACETONE; ISOPROPYL ALCOHOL; METHYL ALCOHOL; METHYLENE CHLORIDE; WATER

ALLEGRA-D® 24 HOUR
(fexofenadine HCl 180 mg and
pseudoephedrine HCl 240 mg)
Extended-Release Tablets

DESCRIPTION

ALLEGRA-D® 24 HOUR (fexofenadine hydrochloride and pseudoephedrine hydrochloride) Extended-Release Tablets for oral administration contain 180 mg fexofenadine hydrochloride for immediate release and 240 mg pseudoephedrine hydrochloride for extended release. Tablets also contain as excipients: microcrystalline cellulose, sodium chloride, cellulose acetate, polyethylene glycol, opadry white, povidone, talc, hypromellose, croscarmellose sodium, copovidone, titanium dioxide, magnesium stearate, colloidal silicon dioxide, brilliant blue aluminum lake, acetone, isopropyl alcohol, methyl alcohol, methylene chloride, water, and black ink.

Fexofenadine hydrochloride, one of the active ingredients of ALLEGRA-D 24 HOUR, is a histamine H1-receptor antagonist with the chemical name (±)-4-[1-hydroxy-4-[4-(hydroxydiphenylmethyl)-1-piperidinyl]-butyl]-α, α-dimethyl benzeneacetic acid hydrochloride and the following chemical structure:

The molecular weight is 538.13 and the empirical formula is C32H39NO4•HCl. Fexofenadine hydrochloride is a white to off-white crystalline powder. It is freely soluble in methanol and ethanol, slightly soluble in chloroform and water, and insoluble in hexane. Fexofenadine hydrochloride is a racemate and exists as a zwitterion in aqueous media at physiological pH.

Pseudoephedrine hydrochloride, the other active ingredient of ALLEGRA-D 24 HOUR, is an adrenergic (vasoconstrictor) agent with the chemical name [S-(R*,R*)]-α-[1-(methylamino)ethyl]-benzenemethanol hydrochloride and the following chemical structure:

The molecular weight is 201.70 and the molecular formula is C10H15NO•HCl. Pseudoephedrine hydrochloride occurs as fine, white to off-white crystals or powder, having a faint characteristic odor. It is very soluble in water, freely soluble in alcohol, and sparingly soluble in chloroform.

CLINICAL PHARMACOLOGY

Mechanism of Action

Fexofenadine hydrochloride, the major active metabolite of terfenadine, is an antihistamine with selective peripheral H1-receptor antagonist activity. Fexofenadine hydrochloride inhibited antigen-induced bronchospasm in sensitized guinea pigs and histamine release from peritoneal mast cells in rats. In laboratory animals, no anticholinergic or alpha1-adrenergic-receptor blocking effects were observed. Moreover, no sedative or other central nervous system effects were observed. Radiolabeled tissue distribution studies in rats indicated that fexofenadine does not cross the blood-brain barrier.

Pseudoephedrine hydrochloride is an orally active sympathomimetic amine and exerts a decongestant action on the nasal mucosa. Pseudoephedrine hydrochloride is recognized as an effective agent for the relief of nasal congestion due to allergic rhinitis. Pseudoephedrine produces peripheral effects similar to those of ephedrine and central effects similar to, but less intense than, amphetamines. It has the potential for excitatory side effects.

Pharmacokinetics

The pharmacokinetics of fexofenadine hydrochloride in subjects with seasonal allergic rhinitis were similar to those in healthy volunteers.

Absorption

Fexofenadine hydrochloride and pseudoephedrine hydrochloride administered as ALLEGRA-D 24 HOUR tablets are absorbed at a similar rate and are equally available under single-dose and steady-state conditions as the separate administration of the components. Coadministration of fexofenadine and pseudoephedrine does not significantly affect the bioavailability of either component. The administration of ALLEGRA-D 24 HOUR tablets 30 minutes or 1.5 hour after a high-fat meal decreased the bioavailability of fexofenadine by approximately 50% (AUC 42% and Cmax 54%). Pseudoephedrine pharmacokinetics were unaffected when coadministered with a high-fat meal. Therefore, ALLEGRA-D 24 HOUR should be taken on an empty stomach with water (see DOSAGE AND ADMINISTRATION).

A pharmacokinetic study following single and multiple oral doses over 7 days of ALLEGRA-D 24 HOUR in 66 healthy volunteers showed that fexofenadine, the immediate release component of ALLEGRA-D 24 HOUR, was rapidly absorbed with mean maximum plasma concentrations of 634 ng/mL and 674 ng/mL after single and multiple doses, respectively. The median time to maximum concentration of fexofenadine was 1.8–2.0 hours post-dose. In the same study, the mean maximum plasma concentrations of pseudoephedrine, the extended-release component of ALLEGRA-D 24 HOUR, were 394 ng/mL and 495 ng/mL after single and multiple doses, respectively, with median time to maximum concentration of 12 hours post-dose. Pseudoephedrine concentrations at the end of the dosing interval (mean: 172 ng/mL) at steady state were equivalent to those observed from a comparator pseudoephedrine hydrochloride 240 mg tablet.

Distribution

Fexofenadine hydrochloride is 60% to 70% bound to plasma proteins, primarily albumin and α1-acid glycoprotein. The protein binding of pseudoephedrine in humans is not known. Pseudoephedrine hydrochloride is extensively distributed into extravascular sites (apparent volume of distribution between 2.6 and 3.5 L/kg).

Metabolism

Approximately 5% of the total dose of fexofenadine hydrochloride and less than 1% of the total oral dose of pseudoephedrine hydrochloride were eliminated by hepatic metabolism.

Elimination

The mean terminal elimination half-life of fexofenadine was 14.6 hours following administration of ALLEGRA-D 24 HOUR tablets in healthy volunteers, which is consistent with observations from separate administration. Human mass balance studies documented a recovery of approximately 80% and 11% of the [^14C]-fexofenadine hydrochloride dose in the feces and urine, respectively. Because the absolute bioavailability of fexofenadine hydrochloride has not been established, it is unknown if the fecal component is primarily unabsorbed drug or the result of biliary excretion. The mean terminal half-life of pseudoephedrine was 7 hours following single-dose administration of ALLEGRA-D 24 HOUR tablets.

Pseudoephedrine has been shown to have a mean elimination half-life of 4–6 hours which is dependent on urine pH. The elimination half-life is decreased at urine pH lower than 6 and may be increased at urine pH higher than 8.

Special Populations

Pharmacokinetics in special populations (for renal, hepatic impairment, and age), obtained after a single dose of 80 mg fexofenadine hydrochloride, were compared to those from healthy volunteers in a separate study of similar design.

Effect of Age

In older subjects (≥65 years old), peak plasma levels of fexofenadine were 99% greater than those observed in younger subjects (<65 years old). Mean fexofenadine elimination half-lives were similar to those observed in younger subjects.

Renally Impaired

In subjects with mild (creatinine clearance 41–80 mL/min) to severe (creatinine clearance 11–40 mL/min) renal impairment, peak plasma levels of fexofenadine were 87% and 111% greater, respectively, and mean elimination half-lives were 59% and 72% longer, respectively, than observed in healthy volunteers. Peak plasma levels in subjects on dialysis (creatinine clearance ≤10 mL/min) were 82% greater and half-life was 31% longer than observed in healthy volunteers. No data are available on the pharmacokinetics of pseudoephedrine in renally impaired subjects. However, most of the oral dose of pseudoephedrine hydrochloride (43–96%) is excreted unchanged in the urine. A decrease in renal function is, therefore, likely to decrease the clearance of pseudoephedrine significantly, thus prolonging the half-life and resulting in accumulation. (See PRECAUTIONS and DOSAGE AND ADMINISTRATION.)

Hepatically Impaired

The pharmacokinetics of fexofenadine hydrochloride in subjects with hepatic disease did not differ substantially from that observed in healthy volunteers. The effect on pseudoephedrine pharmacokinetics is unknown.

Effect of Gender

Across several trials, no clinically significant gender-related differences were observed in the pharmacokinetics of fexofenadine hydrochloride.

Pharmacodynamics

Wheal and Flare

Human histamine skin wheal and flare studies following single and twice daily doses of 20 mg and 40 mg fexofenadine hydrochloride demonstrated that the drug exhibits an antihistamine effect by 1 hour, achieves maximum effect at 2–3 hours, and an effect is still seen at 12 hours. There was no evidence of tolerance to these effects after 28 days of dosing. The clinical significance of these observations is unknown.

Effects on QTc

In dogs (30 mg/kg orally twice daily for 5 days) and rabbits (10 mg/kg intravenously over 1 hour), fexofenadine hydrochloride did not prolong QTc at plasma concentrations that were at least 7 and 15 times, respectively, the therapeutic plasma concentrations in man (based on a 180 mg once daily fexofenadine hydrochloride dose when administered as ALLEGRA-D 24 HOUR). No effect was observed on calcium channel current, delayed K^+ channel current, or action potential duration in guinea pig myocytes, Na^+ current in rat neonatal myocytes, or on the delayed rectifier K^+ channel cloned from human heart at concentrations up to 1 × 10^−5 M of fexofenadine. This concentration was at least 8 times the therapeutic plasma concentration in man (based on a 180 mg once daily fexofenadine hydrochloride dose).

No statistically significant increase in mean QTc interval compared to placebo was observed in 714 subjects with seasonal allergic rhinitis given fexofenadine hydrochloride capsules in doses of 60 mg to 240 mg twice daily for 2 weeks or in 40 healthy volunteers given fexofenadine hydrochloride as an oral solution at doses up to 400 mg twice daily for 6 days.

A 1-year study designed to evaluate safety and tolerability of 240 mg of fexofenadine hydrochloride (n=240) compared to placebo (n=237) in healthy volunteers, did not reveal a statistically significant increase in the mean QTc interval for the fexofenadine hydrochloride treated group when evaluated pretreatment and after 1, 2, 3, 6, 9, and 12 months of treatment.

Administration of the 60 mg fexofenadine hydrochloride/120 mg pseudoephedrine hydrochloride combination tablet for approximately 2 weeks to 213 subjects with seasonal allergic rhinitis demonstrated no statistically significant increase in the mean QTc interval compared to fexofenadine hydrochloride administered alone (60 mg twice daily, n=215), or compared to pseudoephedrine hydrochloride (120 mg twice daily, n=215) administered alone.

Clinical Studies

Clinical efficacy and safety studies were not conducted with ALLEGRA-D 24 HOUR Extended-Release Tablets. The effectiveness of ALLEGRA-D 24 HOUR for the treatment of seasonal allergic rhinitis is based on an extrapolation of the demonstrated efficacy of ALLEGRA 180 mg and the nasal decongestant properties of pseudoephedrine hydrochloride.

In one 2-week, multicenter, randomized, double-blind clinical trial in subjects 12 to 65 years of age with seasonal allergic rhinitis (n=863), fexofenadine hydrochloride 180 mg once daily significantly reduced total symptom scores (the sum of the individual scores for sneezing, rhinorrhea, itchy nose/palate/throat, itchy/watery/red eyes) compared to placebo. Although the number of subjects in some of the subgroups was small, there were no significant differences in the effect of fexofenadine hydrochloride across subgroups of subjects defined by gender, age, and race.

INDICATIONS AND USAGE

ALLEGRA-D 24 HOUR Extended-Release Tablets are indicated for the relief of symptoms associated with seasonal allergic rhinitis in adults and children 12 years of age and older. Symptoms treated effectively include sneezing, rhinorrhea, itchy nose/palate/ and/or throat, itchy/watery/red eyes, and nasal congestion.

ALLEGRA-D 24 HOUR should be administered when both the antihistaminic properties of fexofenadine hydrochloride and the nasal decongestant properties of pseudoephedrine hydrochloride are desired (see CLINICAL PHARMACOLOGY).

CONTRAINDICATIONS

ALLEGRA-D 24 HOUR is contraindicated in patients with known hypersensitivity to any of its ingredients.

Due to its pseudoephedrine component, ALLEGRA-D 24 HOUR is contraindicated in patients with narrow-angle glaucoma or urinary retention, and in patients receiving monoamine oxidase (MAO) inhibitor therapy or within fourteen (14) days of stopping such treatment (see Drug Interactions section). It is also contraindicated in patients with severe hypertension, or severe coronary artery disease, and in those who have shown idiosyncrasy to its components, to adrenergic agents, or to other drugs of similar chemical structures. Manifestations of patient idiosyncrasy to adrenergic agents include: insomnia, dizziness, weakness, tremor, or arrhythmias.

WARNINGS

Sympathomimetic amines should be used with caution in patients with hypertension, diabetes mellitus, ischemic heart disease, increased intraocular pressure, hyperthyroidism, renal impairment, or prostatic hypertrophy (see CONTRAINDICATIONS). Sympathomimetic amines may produce central nervous system stimulation with convulsions or cardiovascular collapse with accompanying hypotension.

PRECAUTIONS

General

Because ALLEGRA-D 24 HOUR is a once-daily, fixed-dose combination that cannot be titrated and renal insufficiency increases the bioavailability and prolongs the half-life of fexofenadine hydrochloride and pseudoephedrine hydrochloride, ALLEGRA-D 24 HOUR tablets should generally be avoided in patients with renal insufficiency (see CLINICAL PHARMACOLOGY, and DOSAGE AND ADMINISTRATION).

Information for Patients

Patients taking ALLEGRA-D 24 HOUR tablets should receive the following information: ALLEGRA-D 24 HOUR tablets are prescribed for the relief of symptoms of seasonal allergic rhinitis. Patients should be instructed to take ALLEGRA-D 24 HOUR tablets only as prescribed. Do not exceed the recommended dose. If nervousness, dizziness, or sleeplessness occur, discontinue use and consult the doctor. Patients should also be advised against the concurrent use of ALLEGRA-D 24 HOUR tablets with over-the-counter antihistamines and decongestants.

The product should not be used by patients who are hypersensitive to it or to any of its ingredients. Due to its pseudoephedrine component, this product should not be used by patients with narrow-angle glaucoma, urinary retention, or by patients receiving a monoamine oxidase (MAO) inhibitor or within 14 days of stopping use of MAO inhibitor. It also should not be used by patients with severe hypertension or severe coronary artery disease.

Patients should be told that this product should be used in pregnancy or lactation only if the potential benefit justifies the potential risk to the fetus or nursing infant. Patients should be advised to take the tablet on an empty stomach with water. Patients should be directed to swallow the tablet whole. Patients should be cautioned not to break or chew the tablet. Patients should also be instructed to store the medication in a tightly closed container in a cool, dry place, away from children.

Drug Interactions

Fexofenadine hydrochloride and pseudoephedrine hydrochloride do not influence the pharmacokinetics of each other when administered concomitantly.

Fexofenadine has been shown to exhibit minimal (ca. 5%) metabolism. However, co-administration of fexofenadine hydrochloride with either ketoconazole or erythromycin led to increased plasma concentrations of fexofenadine. Fexofenadine had no effect on the pharmacokinetics of either erythromycin or ketoconazole. In 2 separate studies, fexofenadine hydrochloride 120 mg twice daily was co-administered with either erythromycin 500 mg every 8 hours or ketoconazole 400 mg once daily under steady-state conditions to healthy volunteers (n=24, each study). No differences in adverse events or QTc interval were observed when subjects were administered fexofenadine hydrochloride alone or in combination with either erythromycin or ketoconazole. The findings of these studies are summarized in the following table:

Effects on steady-state fexofenadine pharmacokinetics after 7 days of co-administration with fexofenadine hydrochloride 120 mg every 12 hours (two times the recommended twice daily dose) in healthy volunteers (n=24)
Concomitant Drug | CmaxSS (Peak plasma concentration) | AUCss(0–12h) (Extent of systemic exposure)
Erythromycin (500 mg every 8 hrs) | +82% | +109%
Ketoconazole (400 mg once daily) | +135% | +164%

The changes in plasma levels were within the range of plasma levels achieved in adequate and well-controlled clinical trials.

The mechanism of these interactions has been evaluated in in vitro, in situ, and in vivo animal models. These studies indicate that ketoconazole or erythromycin co-administration enhances fexofenadine gastrointestinal absorption. This observed increase in the bioavailability of fexofenadine may be due to transport-related effects, such as p-glycoprotein. In vivo animal studies also suggest that in addition to enhancing absorption, ketoconazole decreases fexofenadine gastrointestinal secretion, while erythromycin may also decrease biliary excretion.

Due to the pseudoephedrine component, ALLEGRA-D 24 HOUR is contraindicated in patients taking monoamine oxidase inhibitors and for 14 days after stopping use of an MAO inhibitor. Concomitant use with antihypertensive drugs which interfere with sympathetic activity (e.g., methyldopa, mecamylamine, and reserpine) may reduce their antihypertensive effects. Increased ectopic pacemaker activity can occur when pseudoephedrine is used concomitantly with digitalis. Care should be taken in the administration of ALLEGRA-D 24 HOUR concomitantly with other sympathomimetic amines because combined effects on the cardiovascular system may be harmful to the patient (see WARNINGS).

Drug Interactions with Antacids

Administration of 120 mg of fexofenadine hydrochloride (2 × 60 mg capsule) within 15 minutes of an aluminum and magnesium containing antacid (Maalox®) decreased fexofenadine AUC by 41% and Cmax by 43%. ALLEGRA-D 24 HOUR should not be taken closely in time with aluminum and magnesium containing antacids.

Interactions with Fruit Juices

Fruit juices such as grapefruit, orange and apple may reduce the bioavailability and exposure of fexofenadine. This is based on the results from 3 clinical studies using histamine induced skin wheals and flares coupled with population pharmacokinetic analysis. The size of wheal and flare were significantly larger when fexofenadine hydrochloride was administered with either grapefruit or orange juices compared to water. Based on the literature reports, the same effects may be extrapolated to other fruit juices such as apple juice. The clinical significance of these observations is unknown. In addition, based on the population pharmacokinetics analysis of the combined data from grapefruit and orange juices studies with the bioequivalence study data, the bioavailability of fexofenadine was reduced by 36%. Therefore, to maximize the effects of fexofenadine, it is recommended that ALLEGRA-D 24 HOUR should be taken with water (see DOSAGE AND ADMINISTRATION).

Carcinogenesis, Mutagenesis, Impairment of Fertility

There are no animal or in vitro studies on the combination product fexofenadine hydrochloride and pseudoephedrine hydrochloride to evaluate carcinogenesis, mutagenesis, or impairment of fertility.

The carcinogenic potential and reproductive toxicity of fexofenadine hydrochloride were assessed using terfenadine studies with adequate fexofenadine exposure (area-under-the plasma concentration versus time curve [AUC]). No evidence of carcinogenicity was observed when mice and rats were given daily oral doses up to 150 mg/kg of terfenadine for 18 and 24 months, respectively. In both species, 150 mg/kg of terfenadine produced AUC values of fexofenadine that were approximately 2 and 3 times, respectively, the exposure from the maximum recommended human daily oral dose of ALLEGRA-D 24 HOUR.

Two-year feeding studies in rats and mice conducted under the auspices of the National Toxicology Program (NTP) demonstrated no evidence of carcinogenic potential with ephedrine sulfate, a structurally related drug with pharmacological properties similar to pseudoephedrine, at doses up to 10 and 27 mg/kg, respectively (less than the maximum recommended human daily oral dose of pseudoephedrine hydrochloride on a mg/m^2 basis).

In in vitro (Bacterial Reverse Mutation, CHO/HGPRT Forward Mutation, and Rat Lymphocyte Chromosomal Aberration assays) and in vivo (Mouse Bone Marrow Micronucleus assay) tests, fexofenadine hydrochloride revealed no evidence of mutagenicity.

Reproduction and fertility studies with terfenadine in rats produced no effect on male or female fertility at oral doses up to 300 mg/kg/day (approximately 3 times the maximum recommended human daily oral dose of ALLEGRA-D 24 HOUR based on comparison of the AUCs of fexofenadine). However, reduced implants and post-implantation losses were reported at 300 mg/kg. A reduction in implants was also observed at an oral dose of 150 mg/kg/day (approximately 3 times the maximum recommended human daily oral dose of ALLEGRA-D 24 HOUR based on comparison of the AUCs). In mice, fexofenadine produced no effect on male or female fertility at average dietary doses up to 4438 mg/kg (approximately 10 times the maximum recommended human daily oral dose of ALLEGRA-D 24 HOUR based on comparison of the AUCs).

Pregnancy

Teratogenic Effects

Category C

Terfenadine alone was not teratogenic in rats at oral doses up to 300 mg/kg (approximately 3 times the maximum recommended human daily oral dose of ALLEGRA-D 24 HOUR based on comparison of the AUCs of fexofenadine) and in rabbits at oral doses up to 300 mg/kg (approximately 25 times the maximum recommended human daily oral dose of ALLEGRA-D 24 HOUR based on comparison of the AUCs of fexofenadine).

In mice, no adverse effects and no teratogenic effects during gestation were observed with fexofenadine at dietary doses up to 3730 mg/kg (approximately 10 times the maximum recommended human daily oral dose of ALLEGRA-D 24 HOUR based on comparison of the AUCs).

The combination of terfenadine and pseudoephedrine hydrochloride in a ratio of 1:2 by weight was studied in rats and rabbits. In rats, an oral combination dose of 150/300 mg/kg produced reduced fetal weight and delayed ossification with a finding of wavy ribs. The dose of 150 mg/kg of terfenadine in rats produced an AUC value of fexofenadine that was approximately 3 times the AUC of the maximum recommended human daily oral dose of ALLEGRA-D 24 HOUR. The dose of 300 mg/kg of pseudoephedrine hydrochloride in rats was approximately 10 times the maximum recommended human daily oral dose of ALLEGRA-D 24 HOUR on a mg/m^2 basis. In rabbits, an oral combination dose of 100/200 mg/kg produced decreased fetal weight. By extrapolation, the AUC of fexofenadine for 100 mg/kg orally of terfenadine was approximately 8 times the human AUC of the maximum recommended human daily oral dose of ALLEGRA-D 24 HOUR. The dose of 200 mg/kg of pseudoephedrine hydrochloride was approximately 15 times the maximum recommended human daily oral dose of ALLEGRA-D 24 HOUR on a mg/m^2 basis.

There are no adequate and well-controlled studies in pregnant women. ALLEGRA-D 24 HOUR should be used during pregnancy only if the potential benefit justifies the potential risk to the fetus.

Nonteratogenic Effects

Dose-related decreases in pup weight gain and survival were observed in rats exposed to an oral dose of 150 mg/kg of terfenadine; this dose produced an AUC of fexofenadine that was approximately 3 times the human AUC of the maximum recommended human daily oral dose of ALLEGRA-D 24 HOUR.

Nursing Mothers

It is not known if fexofenadine is excreted in human milk. Because many drugs are excreted in human milk, caution should be used when fexofenadine hydrochloride is administered to a nursing woman. Pseudoephedrine hydrochloride administered alone distributes into breast milk of lactating human females. Pseudoephedrine concentrations in milk are consistently higher than those in plasma. The total amount of drug in milk as judged by AUC is 2 to 3 times greater than the plasma AUC. The fraction of a pseudoephedrine dose excreted in milk is estimated to be 0.4% to 0.7%. A decision should be made whether to discontinue nursing or to discontinue the drug, taking into account the importance of the drug to the mother. Caution should be exercised when ALLEGRA-D 24 HOUR is administered to nursing women.

Pediatric Use

Safety and effectiveness of ALLEGRA-D 24 HOUR in children below the age of 12 years have not been established. In addition, the doses of the individual components in ALLEGRA-D 24 HOUR exceed the recommended individual doses for pediatric patients under 12 years of age. ALLEGRA-D 24 HOUR is not recommended for pediatric patients under 12 years of age.

Geriatric Use

Clinical studies of ALLEGRA-D 24 HOUR did not include sufficient numbers of subjects aged 65 and older to determine whether they respond differently from younger subjects. Other reported clinical experience has not identified differences in responses between the elderly and younger patients, although the elderly are more likely to have adverse reactions to sympathomimetic amines.

The pseudoephedrine component of ALLEGRA-D 24 HOUR is known to be substantially excreted by the kidney, and the risk of toxic reactions to this drug may be greater in patients with impaired renal function. Because elderly patients are more likely to have decreased renal function, it may be useful to monitor renal function.

ADVERSE REACTIONS

Fexofenadine Hydrochloride

In a placebo-controlled clinical study in the United States, which included 570 subjects with seasonal allergic rhinitis aged 12 years and older receiving fexofenadine hydrochloride tablets at doses of 120 or 180 mg once daily, adverse events were similar in fexofenadine hydrochloride and placebo-treated subjects. The following table lists adverse experiences that were reported by greater than 2% of subjects treated with fexofenadine hydrochloride tablets at doses of 180 mg once daily and that were more common with fexofenadine hydrochloride than placebo.

Once daily dosing with fexofenadine hydrochloride tablets at rates of greater than 2%
Adverse experience | Fexofenadine 180 mg once daily (n=283) | Placebo (n=293)
Headache | 10.6% | 7.5%
Upper Respiratory Tract Infection | 3.2% | 3.1%
Back Pain | 2.8% | 1.4%

Events that have been reported during controlled clinical trials involving subjects with seasonal allergic rhinitis at incidences less than 1% and similar to placebo and have been rarely reported during postmarketing surveillance include: insomnia, nervousness, and sleep disorders or paroniria. In rare cases, rash, urticaria, pruritus and hypersensitivity reactions with manifestations such as angioedema, chest tightness, dyspnea, flushing and systemic anaphylaxis have been reported.

Pseudoephedrine Hydrochloride

Pseudoephedrine hydrochloride may cause mild CNS stimulation in hypersensitive patients. Nervousness, excitability, restlessness, dizziness, weakness, or insomnia may occur. Headache, drowsiness, tachycardia, palpitation, pressor activity, cardiac arrhythmias and ischemic colitis have been reported. Sympathomimetic drugs have also been associated with other untoward effects such as fear, anxiety, tenseness, tremor, hallucinations, seizures, pallor, respiratory difficulty, dysuria, and cardiovascular collapse.

OVERDOSAGE

Most reports of fexofenadine hydrochloride overdose contain limited information. However, dizziness, drowsiness, and dry mouth have been reported. For the pseudoephedrine hydrochloride component of ALLEGRA-D 24 HOUR, information on acute overdose is limited to the marketing history of pseudoephedrine hydrochloride. Single doses of fexofenadine hydrochloride up to 800 mg (6 healthy volunteers at this dose level), and doses up to 690 mg twice daily for one month (3 healthy volunteers at this dose level), were administered without the development of clinically significant adverse events.

In large doses, sympathomimetics may give rise to giddiness, headache, nausea, vomiting, sweating, thirst, tachycardia, precordial pain, palpitations, difficulty in micturition, muscular weakness and tenseness, anxiety, restlessness, and insomnia. Many patients can present a toxic psychosis with delusions and hallucinations. Some may develop cardiac arrhythmias, circulatory collapse, convulsions, coma, and respiratory failure.

In the event of overdose, consider standard measures to remove any unabsorbed drug. Symptomatic and supportive treatment is recommended. Following administration of terfenadine, hemodialysis did not effectively remove fexofenadine, the major active metabolite of terfenadine, from blood (up to 1.7% removed). The effect of hemodialysis on the removal of pseudoephedrine is unknown.

No deaths occurred in mature mice and rats at oral doses of fexofenadine hydrochloride up to 5000 mg/kg (approximately 110 and 230 times, respectively, the maximum recommended human daily oral dose of ALLEGRA-D 24 HOUR on a mg/m^2 basis.) The median oral lethal dose in newborn rats was 438 mg/kg (approximately 20 times the maximum recommended human daily oral dose of ALLEGRA-D 24 HOUR on a mg/m^2 basis). In dogs, no evidence of toxicity was observed at oral doses up to 2000 mg/kg (approximately 300 times the maximum recommended human daily oral dose of ALLEGRA-D 24 HOUR on a mg/m^2 basis). The oral median lethal dose of pseudoephedrine hydrochloride in rats was 1674 mg/kg (approximately 55 times the maximum recommended human daily oral dose of ALLEGRA-D 24 HOUR on a mg/m^2 basis).

DOSAGE AND ADMINISTRATION

The recommended dose of ALLEGRA-D 24 HOUR Extended-Release Tablets is one tablet once daily administered on an empty stomach with water for adults and children 12 years of age and older. ALLEGRA-D 24 HOUR tablets should generally be avoided in patients with renal insufficiency. ALLEGRA-D 24 HOUR must be swallowed whole and never crushed or chewed.

HOW SUPPLIED

ALLEGRA-D 24 HOUR Extended-Release Tablets contain 180 mg fexofenadine hydrochloride for immediate release and 240 mg pseudoephedrine hydrochloride for extended release. ALLEGRA-D 24 HOUR Extended-Release Tablets are available in high-density polyethylene (HDPE) of:

Bottles of 10 | NDC 54868-5419-0
Bottles of 30 | NDC 54868-5419-1

All bottles have a polypropylene screw cap containing a pulp/wax liner with heat-sealed foil inner seal.

ALLEGRA-D 24 HOUR Extended-Release Tablet is a white, round, film coated tablet. The tablet has 308AV printed on one side in black ink.

Store ALLEGRA-D 24 HOUR Extended-Release Tablets at 20–25°C (68–77°F). (See USP Controlled Room Temperature.)

Rev. December 2009

sanofi-aventis U.S. LLC
Bridgewater, NJ 08807

©2009 sanofi-aventis U.S. LLC

Relabeling and Repackaging by:
Physicians Total Care, Inc.
Tulsa, OK 74146

PRINCIPAL DISPLAY PANEL - Bottle Label

allegra-D 24 Hour

fexofenadine HCl 180mg and
pseudoephedrine HCl 240mg

Extended-Release Tablets

Rx ONLY